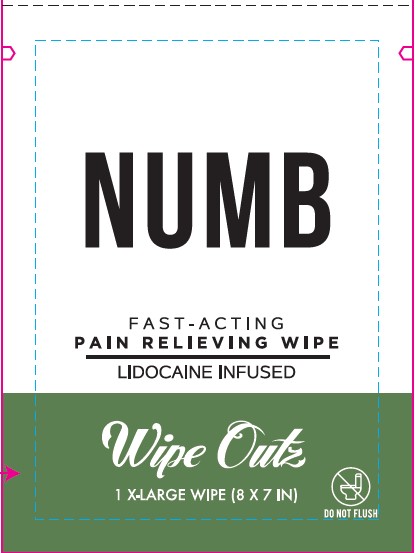 DRUG LABEL: Lidocaine Tattoo Wipe
NDC: 85055-397 | Form: CLOTH
Manufacturer: MD Tattoo Company
Category: otc | Type: HUMAN OTC DRUG LABEL
Date: 20250523

ACTIVE INGREDIENTS: LIDOCAINE HYDROCHLORIDE 3 g/100 g
INACTIVE INGREDIENTS: BENZALKONIUM CHLORIDE; POLYSORBATE 20; CAPRYLYL GLYCOL; PHENOXYETHANOL; WATER

NUMB FAST- ACTING PAIN RELIEVING WIPE

Active Ingredient

LIDOCAINE HCI 3% w/w

Purpose

Pain reliever

Uses

• For temporarily relief of pain and itching associated with minor • cuts • burns • sunburns • insect bites • scrapes • and minor skin irritations

Warnings

• For external use only.

Ask a doctor if you have • deep puncture wounds • animal bites • serious burns.

When using this product • do not use in or near the eyes • in case of contact, rinse eyes thoroughly with water • do not apply over large areas of the body or in large quantities.

Stop use and ask a doctor if • condition worsens • irritation or rash appears and lasts for more than 72 hours.

Keep out of reach of children. If swallowed, get medical help or contact the Poison Control Center right away.

Directions

• For adults and Children two years and older: Apply the wipe thoroughly to the affected area. Use up to 3-4 times daily. For best results, allow the area to remain wet for 1-2 minutes.

Inactive Ingredients

• Benzalkonium Chloride, Caprylyl Glycol, Phenoxyethanol, Polysorbate 20, Water.

Principal Display Panel

NUMB

FAST-ACTING

PAIN RELIEVING WIPE

LIDOCAINE INFUSED

Wipe Outz

1 X-LARGE WIPE (8 X 7 IN)

DO NOT FLUSH